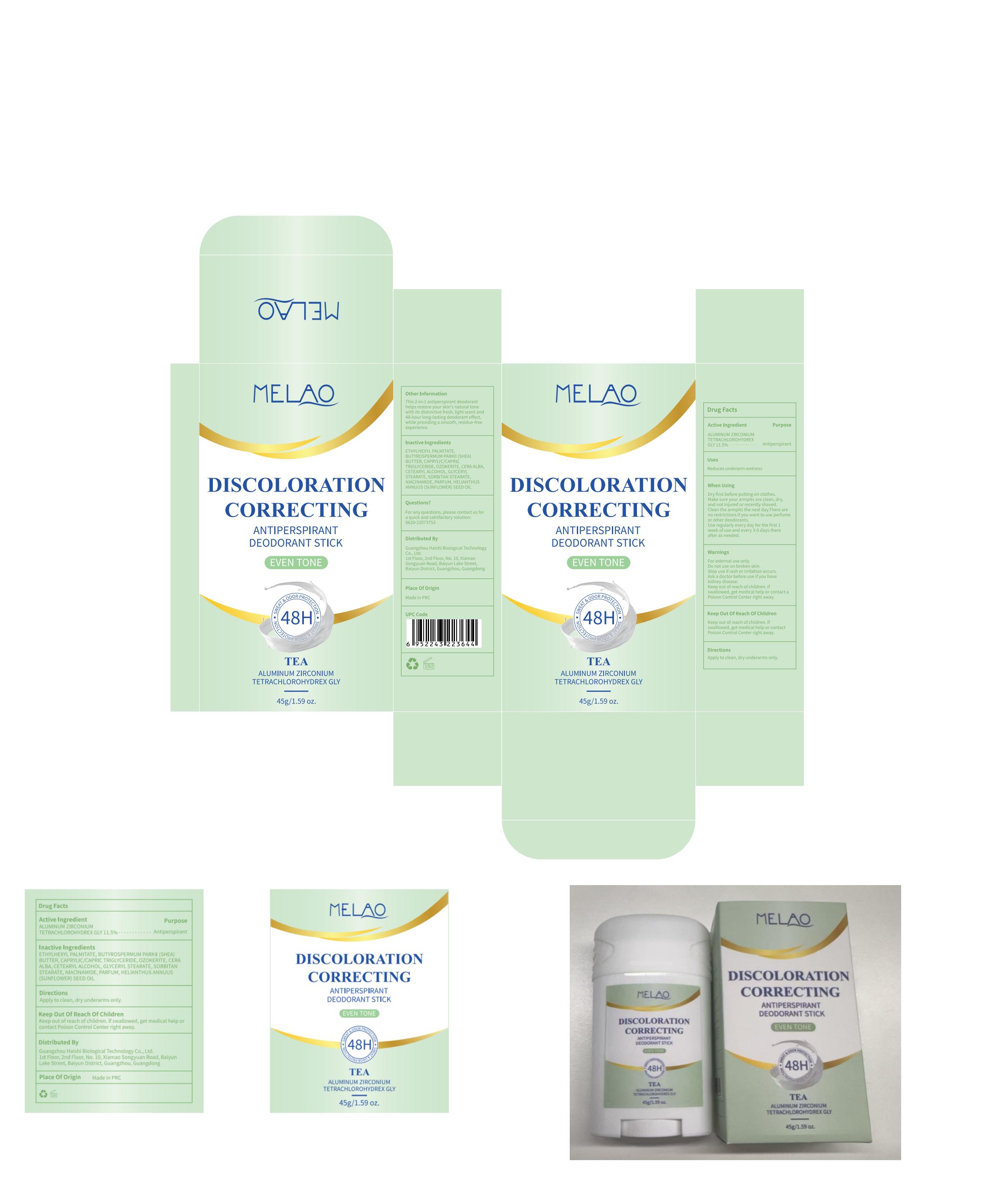 DRUG LABEL: MELAO Discoloration Correcting Antiperspirant Deodorant Stick(tea)
NDC: 60771-0016 | Form: STICK
Manufacturer: Guangzhou Haishi Biological Technology Co., Ltd.
Category: otc | Type: HUMAN OTC DRUG LABEL
Date: 20250527

ACTIVE INGREDIENTS: ALUMINUM ZIRCONIUM TETRACHLOROHYDREX GLY 11.5 g/100 g
INACTIVE INGREDIENTS: SORBITAN STEARATE; ETHYLHEXYL PALMITATE; NIACINAMIDE; CETEARYL ALCOHOL; HELIANTHUS ANNUUS (SUNFLOWER) SEED OIL; CAPRYLIC/CAPRIC TRIGLYCERIDE; GLYCERYL STEARATE

MELAO DISCOLORATION CORRECTING ANTIPERSPIRANT DEODORANT STICK(TEA)

ACTIVE INGREDIENT

ALUMINUM ZIRCONIUM TETRACHLOROHYDREX GLY 11.5%

PURPOSE

Antiperspirant

INDICATIONS AND USAGE

STEP1: Clean and thoroughly dry your skin.

STEP2: Twist the bottom of the product.

STEP3: Gently apply to the underarms or other desired areas.

WARNINGS

For external use only.

Ask a doctor before use if you havekidney disease.

if swallowed, get medical help or contact a Poison Control Center right away.

Stop use if rash or irritation occurs.

Do not use on broken skin.

WHEN USING

Dry first before putting on clothes.Make sure your armpits are clean, dry,and not iniured or recently shaved.Clean the armpits the next day.Thereare no restrictions if you want to useperfume or other deodorants

Keep out of reach of children

DOSAGE AND ADMINISTRATION

Use regularly every day for the first 1week of use and every 3-5 days thereafter as needed.

INACTIVE INGREDIENT

OZOKERITE10%
CETEARYL ALCOHOL4%
BUTYROSPERMUM PARKII(SHEA)BUTTER15%
CAPRYLIC/CAPRIC TRIGLYCERIDE12%
ETHYLHEXYL PALMITATE27.5%
GLYCERYL STEARATE4%
SORBITAN STEARATE4%
CERA ALBA6%
HELIANTHUS ANNUUS (SUNFLOWER) SEED OIL1%
NIACINAMIDE3%
PARFUM2%